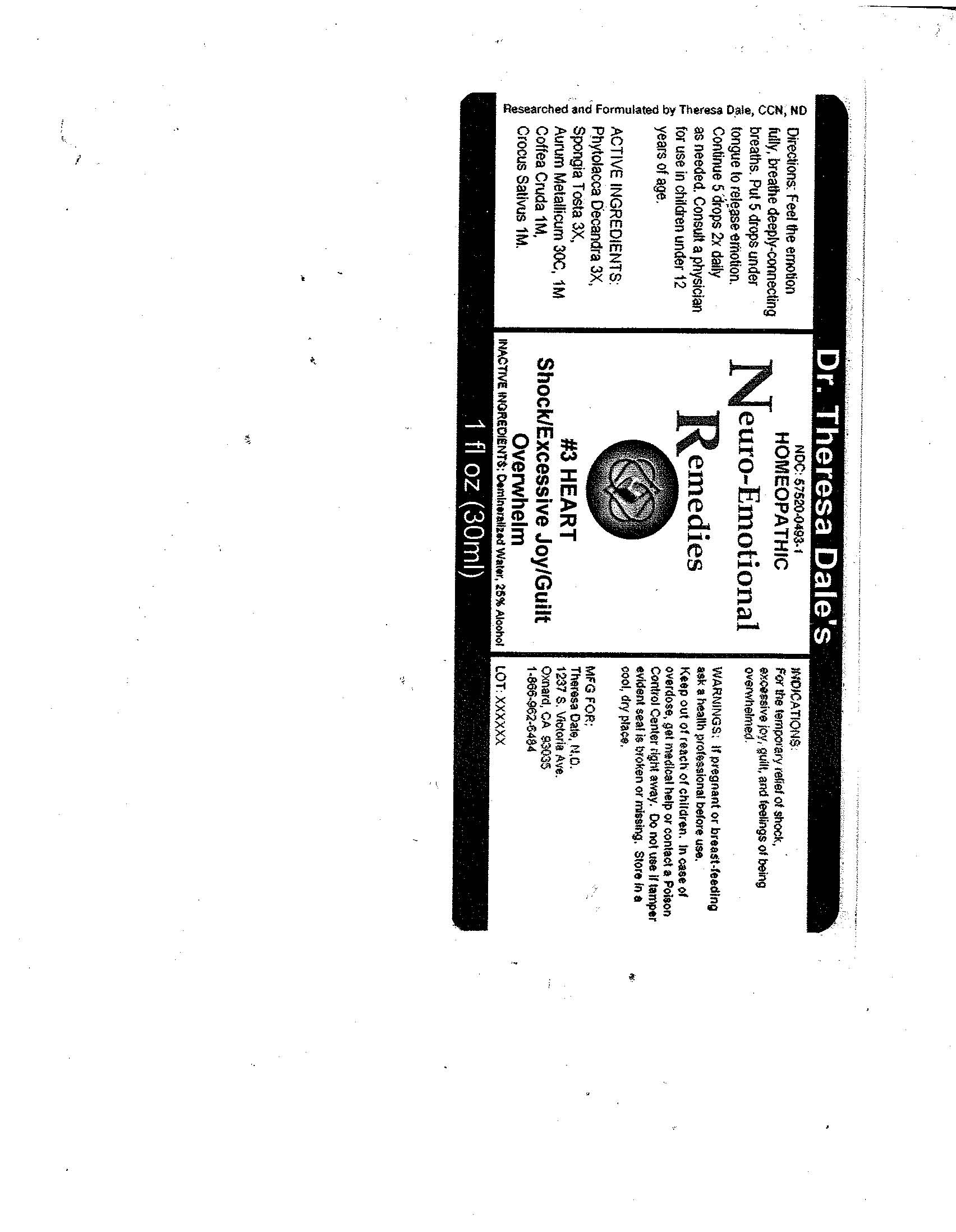 DRUG LABEL: 3 Heart
NDC: 57520-0493 | Form: LIQUID
Manufacturer: Apotheca Company
Category: homeopathic | Type: HUMAN OTC DRUG LABEL
Date: 20100726

ACTIVE INGREDIENTS: PHYTOLACCA AMERICANA ROOT 3 [hp_X]/1 mL; SPONGIA OFFICINALIS SKELETON, ROASTED 3 [hp_X]/1 mL; GOLD 1 [hp_M]/1 mL; ARABICA COFFEE BEAN 1 [hp_M]/1 mL; SAFFRON 1 [hp_M]/1 mL
INACTIVE INGREDIENTS: WATER; ALCOHOL

3 Heart

ACTIVE INGREDIENT

ACTIVE INGREDIENTS: Phytolacca decandra 3X, Spongia tosta 3X, Aurum metallicum 30C, 1M, Coffea cruda 1M, Crocus sativus 1M.

PURPOSE

INDICATIONS: For the temporary relief of shock, excessive joy, guilt and feelings of being overwhelmed.

WARNINGS

WARNINGS: If pregnant or breast-feeding, ask a health professional before use.

Keep out of reach of children. In case of overdose, get medical help or contact a Poison Control Center right away.

Do not use if tamper evident seal is broken or missing. Store in a cool, dry place.

DOSAGE AND ADMINISTRATION

DIRECTIONS: Feel the emotion fully, breathe deeply-connecting breaths. Put 5 drops under tongue to release emotion. Continue 5 drops 2X daily as needed. Consult a physician for use in children under 12 years of age.

INACTIVE INGREDIENTS: Demineralized water, 25% Alcohol.

QUESTIONS

MFG. FOR:

Theresa Dale N.D.

1237 S. Victoria Ave.

Oxnard, CA 83035

1-866-962-6484

PACKAGE LABEL

Dr. Theresa Dale's

HOMEOPATHIC

Neuro-Emotional Remedies

#3 HEART

Shock/Excessive Joy/Guilt Overwhelm

1 fl oz (30 ml)